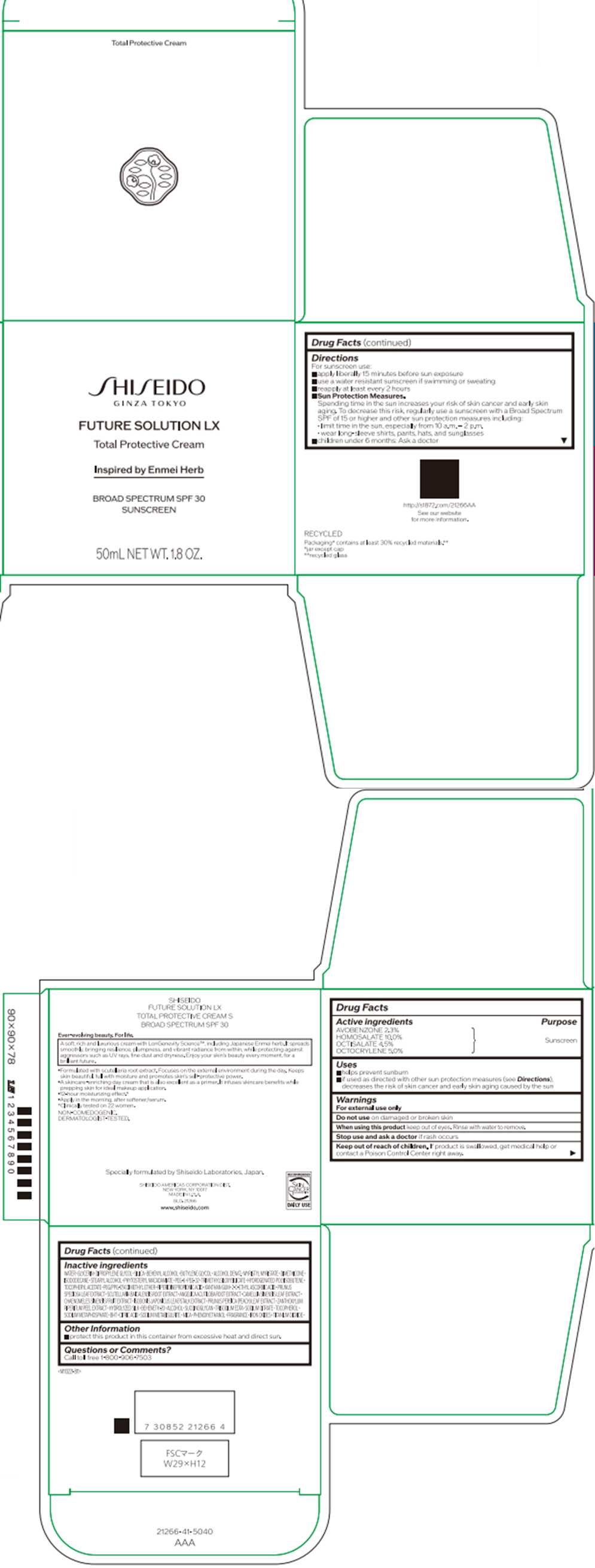 DRUG LABEL: SHISEIDO FUTURE solution LX TOTAL PROTECTIVE S
NDC: 58411-893 | Form: CREAM
Manufacturer: SHISEIDO AMERICAS CORPORATION
Category: otc | Type: HUMAN OTC DRUG LABEL
Date: 20250313

ACTIVE INGREDIENTS: AVOBENZONE 1.18565 g/50 mL; HOMOSALATE 5.155 g/50 mL; OCTISALATE 2.31975 g/50 mL; OCTOCRYLENE 2.5775 g/50 mL
INACTIVE INGREDIENTS: WATER; GLYCERIN; DIPROPYLENE GLYCOL; SILICON DIOXIDE; DOCOSANOL; MYRISTYL MYRISTATE; DIMETHICONE; ISODODECANE; STEARYL ALCOHOL; PHYTOSTERYL MACADAMIATE; POLYETHYLENE GLYCOL 300; POLYETHYLENE GLYCOL 1600; TRIMETHYLSILOXYSILICATE (M/Q 0.6-0.8); HYDROGENATED POLYISOBUTENE (1300 MW); .ALPHA.-TOCOPHEROL ACETATE, DL-; PEG/PPG-17/4 DIMETHYL ETHER; PIPERIDINEPROPIONIC ACID; XANTHAN GUM; 2-O-ETHYL ASCORBIC ACID; PRUNUS SPECIOSA LEAF; SCUTELLARIA BAICALENSIS ROOT; ANGELICA ACUTILOBA ROOT; GREEN TEA LEAF; CHAENOMELES SINENSIS FRUIT; PRUNUS PERSICA LEAF; ZANTHOXYLUM PIPERITUM FRUIT RIND; BEHENETH-20; ALCOHOL; EDETATE TRISODIUM; SODIUM CITRATE, UNSPECIFIED FORM; .ALPHA.-TOCOPHEROL; SODIUM METAPHOSPHATE; BUTYLATED HYDROXYTOLUENE; CITRIC ACID MONOHYDRATE; SODIUM METABISULFITE; MICA; PHENOXYETHANOL; FERRIC OXIDE RED; FERRIC OXIDE YELLOW; FERROSOFERRIC OXIDE; TITANIUM DIOXIDE

SHISEIDO FUTURE SOLUTION LX TOTAL PROTECTIVE CREAM S

Drug Facts

ACTIVE INGREDIENT

Active ingredients | Purpose
AVOBENZONE 2.3% | Sunscreen
HOMOSALATE 10.0% | Sunscreen
OCTISALATE 4.5% | Sunscreen
OCTOCRYLENE 5.0% | Sunscreen

Uses

- helps prevent sunburn
- if used as directed with other sun protection measures (see Directions), decreases the risk of skin cancer and early skin aging caused by the sun

Warnings

For external use only

Do not use on damaged or broken skin

When using this product keep out of eyes. Rinse with water to remove.

Stop use and ask a doctor if rash occurs.

Keep out of reach of children. If product is swallowed, get medical help or contact a Poison Control Center right away.

Directions

For sunscreen use:

- apply liberally 15 minutes before sun exposure
- use a water resistant sunscreen if swimming or sweating
- reapply at least every 2 hours
- Sun Protection Measures. Spending time in the sun increases your risk of skin cancer and early skin aging. To decrease this risk, regularly use a sunscreen with a Broad Spectrum SPF of 15 or higher and other sun protection measures including:
  - limit time in the sun, especially from 10 a.m. – 2 p.m.
  - wear long-sleeve shirts, pants, hats, and sunglasses
- children under 6 months: Ask a doctor

Inactive Ingredients

WATER∙GLYCERIN∙DIPROPYLENE GLYCOL∙SILICA∙BEHENYL ALCOHOL∙BUTYLENE GLYCOL∙ALCOHOL DENAT.∙MYRISTYL MYRISTATE∙DIMETHICONE∙ISODODECANE∙STEARYL ALCOHOL∙PHYTOSTERYL MACADAMIATE∙PEG-6∙PEG-32∙TRIMETHYLSILOXYSILICATE∙HYDROGENATED POLYISOBUTENE∙TOCOPHERYL ACETATE∙PEG/PPG-17/4 DIMETHYL ETHER∙PIPERIDINEPROPIONIC ACID∙XANTHAN GUM∙2-O-ETHYL ASCORBIC ACID∙PRUNUS SPECIOSA LEAF EXTRACT∙SCUTELLARIA BAICALENSIS ROOT EXTRACT∙ANGELICA ACUTILOBA ROOT EXTRACT∙CAMELLIA SINENSIS LEAF EXTRACT∙CHAENOMELES SINENSIS FRUIT EXTRACT∙ISODONIS JAPONICUS LEAF/STALK EXTRACT∙PRUNUS PERSICA (PEACH) LEAF EXTRACT∙ZANTHOXYLUM PIPERITUM PEEL EXTRACT∙HYDROLYZED SILK∙BEHENETH-20∙ALCOHOL∙SUCCINOGLYCAN∙TRISODIUM EDTA∙SODIUM CITRATE∙TOCOPHEROL∙SODIUM METAPHOSPHATE∙BHT∙CITRIC ACID∙SODIUM METABISULFITE∙MICA∙PHENOXYETHANOL∙FRAGRANCE∙IRON OXIDES∙TITANIUM DIOXIDE∙

Other information

- protect this product in this container from excessive heat and direct sun.

Questions or comments?

Call toll free 1-800-906-7503

PRINCIPAL DISPLAY PANEL - 50 mL Jar Carton

SHISEIDO
GINZA TOKYO

FUTURE SOLUTION LX

Total Protective Cream

Inspired by Enmei Herb

BROAD SPECTRUM SPF 30
SUNSCREEN

50mL NET WT. 1.8 OZ.